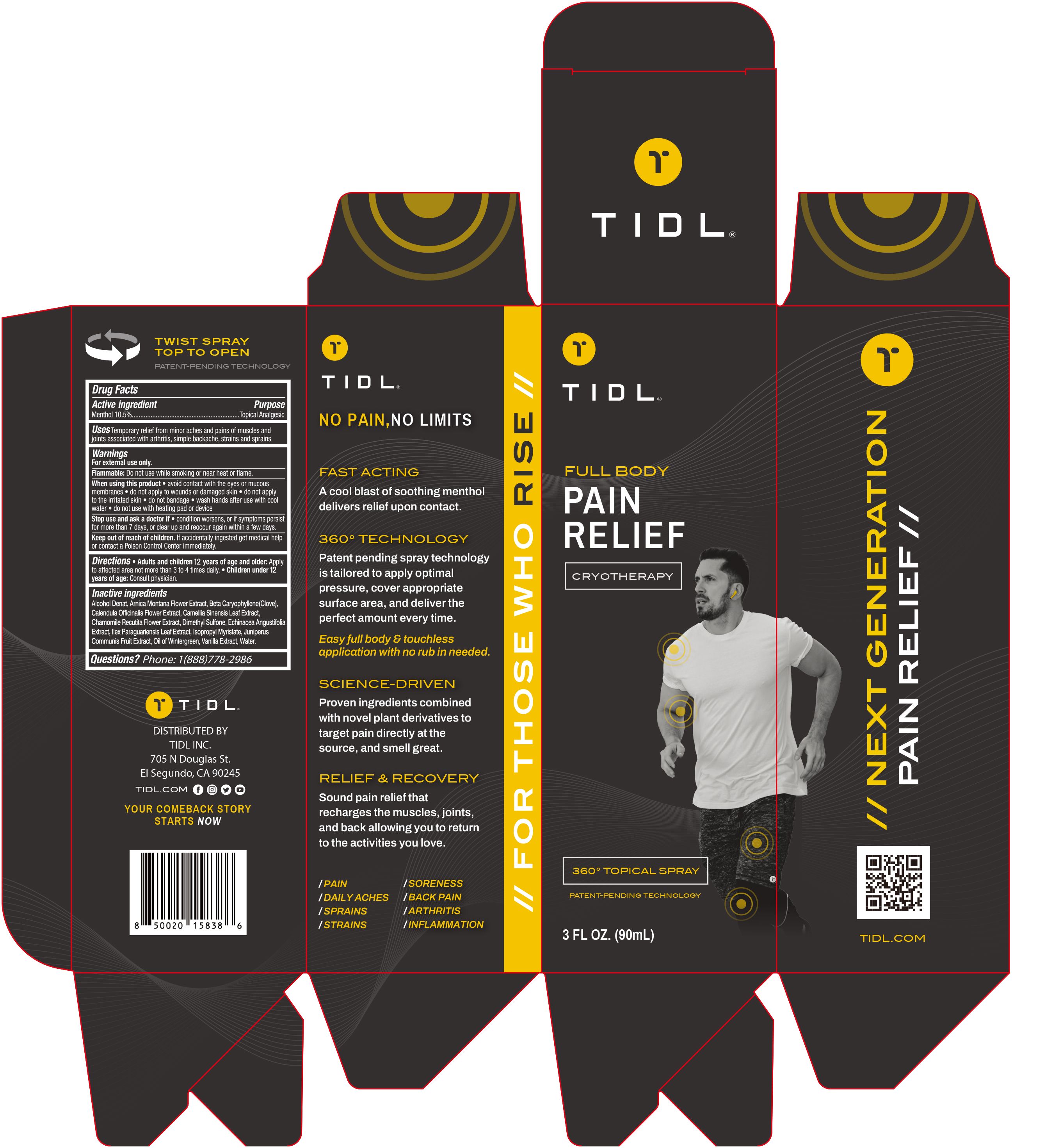 DRUG LABEL: Tidl Full Body Pain Relief Cryotherapy Spray.
NDC: 79740-012 | Form: LIQUID
Manufacturer: The Anthos Group, Inc
Category: otc | Type: HUMAN OTC DRUG LABEL
Date: 20231204

ACTIVE INGREDIENTS: MENTHOL 10.5 g/100 mL
INACTIVE INGREDIENTS: JUNIPER BERRY; CALENDULA OFFICINALIS FLOWER; ECHINACEA ANGUSTIFOLIA; ISOPROPYL MYRISTATE; CHAMOMILE; ILEX PARAGUARIENSIS LEAF; VANILLA; METHYL SALICYLATE; GREEN TEA LEAF; WATER; CARYOPHYLLENE; ALCOHOL; ARNICA MONTANA FLOWER; DIMETHYL SULFONE

Active Ingredient

Menthol 10.5%

Purpose

Topical Analgesic

Use

Temporary relief from minor aches and pains of muscles and joints associated with arthritis，simple backache，strains and sprains

Warnings

For external use only

Do not use

While smoking or near heat or flame

When Using

·avoid contact with the eyes or mucous membranes
·do not apply to wounds or damaged skin
·do not apply to irritated skin
·do not bandage
·wash hands after use with cool water
·do not use with heating pad or device

Stop Use

if condition worsens, or if symptoms persist for more than 7 days, or clear up and reoccur again within a few days

Ask Doctor

if condition worsens, or if symptoms persist for more than 7 days, or clear up and reoccur again within a few days

Keep Oot Of Reach Of Children

If accidentally ingested get medical help or contact a Poison Control Center immediately

Directions

·Adults and children 12 years of age and older：Apply to affected area not more than 3 to 4 times daily
·Children under 12 years of age：Consult physician

Inactive ingredients

Alcohol Denat, Arnica Montana Flower Extract, Beta-Caryophyllene（Clove）, Calendula Officinalis Flower Extract, Camellia Sinensis Leaf Extract, Chamomile Recutita Flower Extract, Dimethyl Sulfone, Echinacea Angustifolia Extract, Ilex Paraguariensis Leaf Extract, Isopropyl Myristate, Juniperus Communis Fruit Extract, Oil of Wintergreen, Vanilla Extract, Water

Questions

Phone：1（888）778-2986